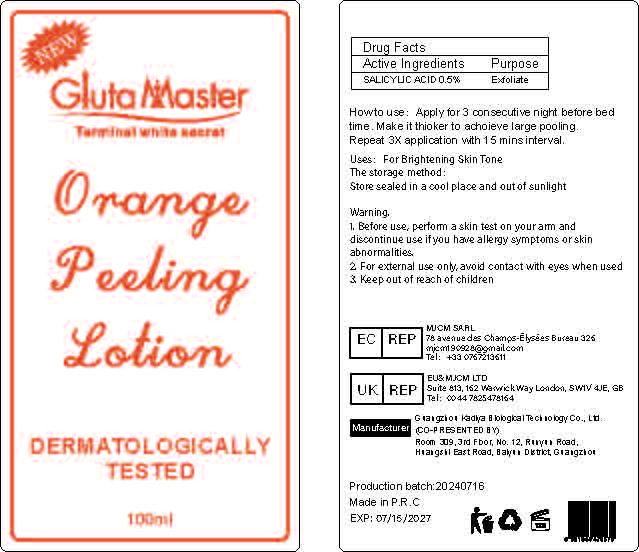 DRUG LABEL: Exfoliating BodyLotion
NDC: 84423-029 | Form: EMULSION
Manufacturer: Guangzhou Kadiya Biotechnology Co., Ltd.
Category: otc | Type: HUMAN OTC DRUG LABEL
Date: 20240724

ACTIVE INGREDIENTS: SALICYLIC ACID 0.25 mg/100 mL
INACTIVE INGREDIENTS: NIACINAMIDE; MINERAL OIL; DMDM HYDANTOIN; ETHYLHEXYL PALMITATE; MYRISTYL MYRISTATE; DIMETHICONE; PROPYLPARABEN; GLYCERYL MONOSTEARATE; PALMITIC ACID; WATER; LAURIC ACID; SODIUM HYDROXIDE; GLYCERIN; PEG-100 STEARATE; CETOSTEARYL ALCOHOL; CARBOXYPOLYMETHYLENE

Uses：
For exfoliation and whitening

INACTIVE INGREDIENT

AQUA、MINERAL OIL、GLYCERIN、ETHYLHEXYL PALMITATE、GLYCERYL STEARATE、LAURIC ACID、MYRISTYL MYRISTATE、PALMITIC ACID、PEG-100 STEARATE、CETEARYL ALCOHOL、DIMETHICONE、NIACINAMIDE、DMDM HYDANTOIN、CARBOMER、PROPYLPARABEN、SODIUM HYDROXIDE

Warning.
1.Before use, perform a skin test on your arm and discontinue use if you have allergy symptoms or skin abnormalities.
2、For external use only, avoid contact with eyes when used
3、Keep out of reach of children

INDICATIONS AND USAGE

Apply for 3 consecutive night before bedtime. Make it thioker to achoieve large pooling. Repeat 3X application with 15 mins interval.

KEEP OUT OF REACH OF CHILDREN SECTION

Active Ingredients
SALICYLIC ACID 0.5%

DOSAGE AND ADMINISTRATION

Apply for 3 consecutive night before bedtime. Make it thioker to achoieve large pooling. Repeat 3X application with 15 mins interval.

PACKAGE LABEL

Active Ingredients
SALICYLIC ACID 0.5%
Uses：
For exfoliation and whitening
The storage method：
Store sealed in a cool place and out of sunlight
Warning.
1.Before use, perform a skin test on your arm and discontinue use if you have allergy symptoms or skin abnormalities.
2、For external use only, avoid contact with eyes when used
3、Keep out of reach of children
Inactive ingredients：
AQUA、MINERAL OIL、GLYCERIN、ETHYLHEXYL PALMITATE、GLYCERYL STEARATE、LAURIC ACID、MYRISTYL MYRISTATE、PALMITIC ACID、PEG-100 STEARATE、CETEARYL ALCOHOL、DIMETHICONE、NIACINAMIDE、DMDM HYDANTOIN、CARBOMER、PROPYLPARABEN、SODIUM HYDROXIDE